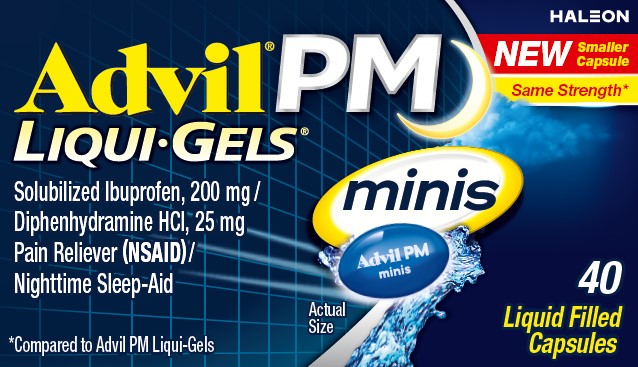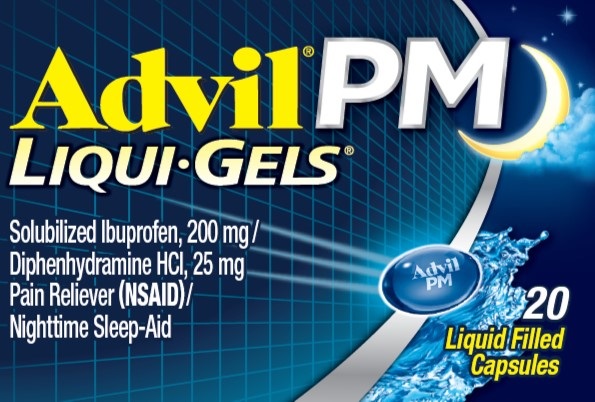 DRUG LABEL: ADVIL PM
NDC: 0573-0167 | Form: CAPSULE, LIQUID FILLED
Manufacturer: Haleon US Holdings LLC
Category: otc | Type: HUMAN OTC DRUG LABEL
Date: 20250115

ACTIVE INGREDIENTS: DIPHENHYDRAMINE HYDROCHLORIDE 25 mg/1 1; IBUPROFEN 200 mg/1 1
INACTIVE INGREDIENTS: D&C RED NO. 33; FD&C BLUE NO. 1; GELATIN, UNSPECIFIED; MEDIUM-CHAIN TRIGLYCERIDES; POLYETHYLENE GLYCOL, UNSPECIFIED; POTASSIUM HYDROXIDE; WATER; SORBITAN; SORBITOL

Drug Facts

Active ingredients (in each capsule)

Diphenhydramine hydrochloride 25 mg

Solubilized ibuprofen equal to 200 mg ibuprofen (NSAID)*

(present as the free acid and potassium salt)

*nonsteroidal anti-inflammatory drug

Purposes

Nighttime sleep-aid

Pain reliever

Uses

- for relief of occasional sleeplessness when associated with minor aches and pains
- helps you fall asleep and stay asleep

Warnings

Allergy alert:

Ibuprofen may cause a severe allergic reaction, especially in people allergic to aspirin. Symptoms may include:

- hives
- facial swelling
- asthma (wheezing)
- shock
- skin reddening
- rash
- blisters

If an allergic reaction occurs, stop use and seek medical help right away.

Stomach bleeding warning:

This product contains an NSAID, which may cause severe stomach bleeding. The chance is higher if you

- are age 60 or older
- have had stomach ulcers or bleeding problems
- take a blood thinning (anticoagulant) or steroid drug
- take other drugs containing prescription or nonprescription NSAIDs [aspirin, ibuprofen, naproxen, or others]
- have 3 or more alcoholic drinks every day while using this product
- take more or for a longer time than directed

Heart attack and stroke warning:

NSAIDs, except aspirin, increase the risk of heart attack, heart failure, and stroke. These can be fatal. The risk is higher if you use more than directed or for longer than directed.

Do not use

- if you have ever had an allergic reaction to any other pain reliever/fever reducer
- unless you have time for a full night's sleep
- in children under 12 years of age
- right before or after heart surgery
- with any other product containing diphenhydramine, even one used on skin
- if you have sleeplessness without pain

Ask a doctor before use if

- stomach bleeding warning applies to you
- you have problems or serious side effects from taking pain relievers or fever reducers
- you have a history of stomach problems, such as heartburn
- you have high blood pressure, heart disease, liver cirrhosis, kidney disease, asthma, or had a stroke.
- you are taking a diuretic
- you have a breathing problem such as emphysema or chronic bronchitis
- you have glaucoma
- you have trouble urinating due to an enlarged prostate gland

Ask a doctor or pharmacist before use if you are

- taking sedatives or tranquilizers, or any other sleep-aid
- under a doctor's care for any continuing medical illness
- taking any other antihistamines
- taking aspirin for heart attack or stroke, because ibuprofen may decrease this benefit of aspirin
- taking any other drug

When using this product

- drowsiness will occur
- avoid alcoholic drinks
- do not drive a motor vehicle or operate machinery
- take with food or milk if stomach upset occurs

Stop use and ask a doctor if

- you experience any of the following signs of stomach bleeding:
  - feel faint
  - vomit blood
  - have bloody or black stools
  - have stomach pain that does not get better
- you have symptoms of heart problems or stroke:
  - chest pain
  - trouble breathing
  - weakness in one part or side of body
  - slurred speech
  - leg swelling
- pain gets worse or lasts more than 10 days
- sleeplessness persists continuously for more than 2 weeks. Insomnia may be a symptom of a serious underlying medical illness.
- redness or swelling is present in the painful area
- any new symptoms appear

If pregnant or breast-feeding,

ask a health professional before use. It is especially important not to use ibuprofen at 20 weeks or later in pregnancy unless definitely directed to do so by a doctor because it may cause problems in the unborn child or complications during delivery.

Keep out of reach of children.

In case of overdose, get medical help or contact a Poison Control Center right away.

Directions

- do not take more than directed
- adults and children 12 years and over: take 2 capsules at bedtime
- do not take more than 2 capsules in 24 hours

Other information

- each capsule contains: potassium 20 mg
- read all warnings and directions before use. Keep carton.
- store at 20-25°C (68-77°F)
- avoid excessive heat above 40°C (104°F)
- protect from light

Inactive ingredients

D&C red no. 33, FD&C blue no. 1, gelatin, medium-chain triglycerides, pharmaceutical ink, polyethylene glycol, potassium hydroxide, purified water, sorbitol sorbitan solution

Questions or Comments?

Call weekdays 9 AM to 5 PM EST at 1-800-88-ADVIL

Additional Information

Do Not Use if seal under bottle cap imprinted with
“SEALED for YOUR PROTECTION” is broken or missing.

For most recent product information, visit www.Advil.com

Dist. by: Haleon, Warren, NJ 07059

Trademarks owned or licensed to the Haleon group of companies.

© 2024 Haleon group of companies or its licensor.

Patents: www.productpats.com

LIQUI-GELS is a trademark or registered trademark

of Catalent Pharma Solutions.

PRINCIPAL DISPLAY PANEL (Advil PM Liqui-Gels)

Advil® PM
LIQUI•GELS®

Solubilized Ibuprofen, 200 mg /
Diphenhydramine HCl, 25 mg
Pain Reliever (NSAID)/
Nighttime Sleep-Aid

20
Liquid Filled
Capsules

Principal Display Panel (Advil PM Liqui-Gels Minis)

Advil® PM
LIQUI•GELS® minis

NEWSmaller Capsule
Same Strength*

Solubilized Ibuprofen, 200 mg /
Diphenhydramine HCl, 25 mg
Pain Reliever (NSAID)/
Nighttime Sleep-Aid

*Compared to Advil PM Liqui-Gels

40
Liquid Filled
Capsules